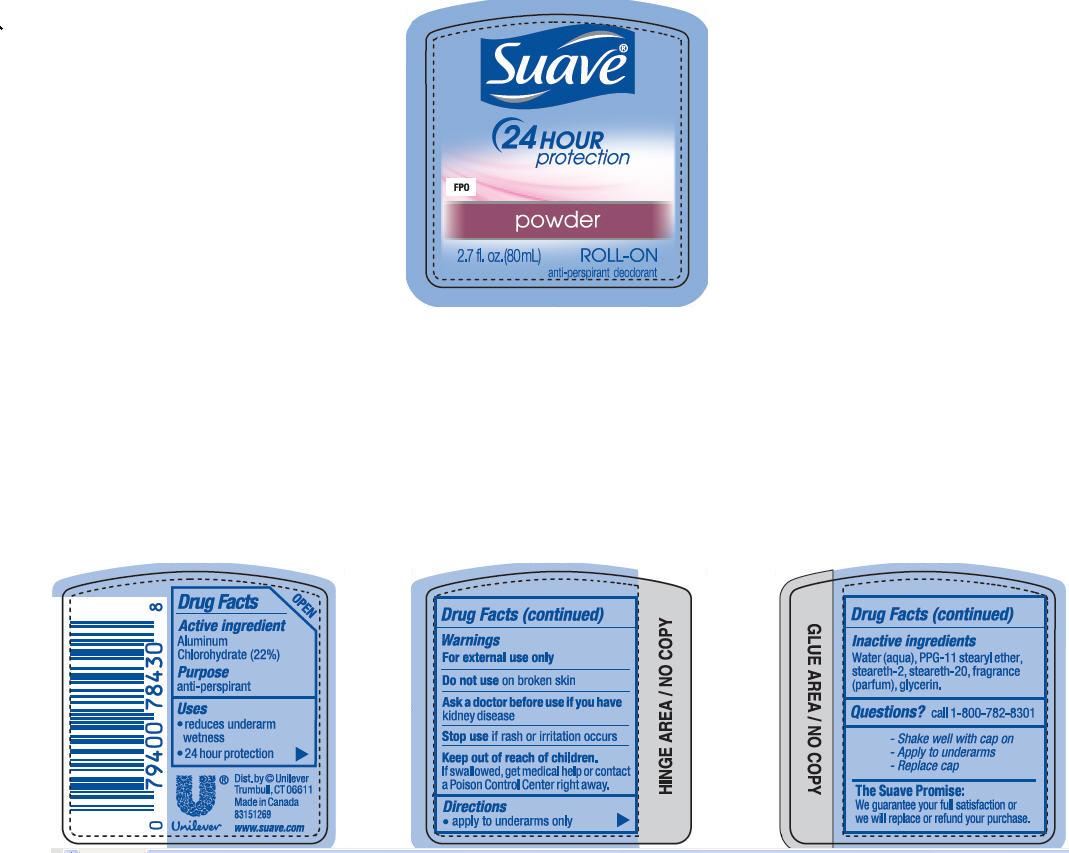 DRUG LABEL: Suave
NDC: 64942-1139 | Form: LIQUID
Manufacturer: Conopco Inc. d/b/a Unilever
Category: otc | Type: HUMAN OTC DRUG LABEL
Date: 20101118

ACTIVE INGREDIENTS: Aluminum Chlorohydrate 22 mL/100 mL
INACTIVE INGREDIENTS: WATER; STEARETH-2; STEARETH-20; GLYCERIN

Suave Powder Roll-On antiperspirant deodorant

Active Ingredient

Aluminum Chlorohydrate (22%)

Purpose
anti-perspirant

Uses
reduces underarm wetness
24 hour protection

Warnings
For External Use Only

Do not use on broken skin

Ask a doctor before use if you have kidney disease

Stop use if rash or irritation occurs

Keep out of reach of children. If swallowed, get medical help or contact a Poison Control Center right away

DOSAGE AND ADMINISTRATION

Directions apply to underarms only

Inactive ingredients
Water (Aqua)
PPG-11 Stearyl Ether
Steareth-2
Steareth-20
Fragrance (Parfum)
Glycerin

Questions? Call 1-800-782-8301

PACKAGE LABEL

2.7 fl oz PDP